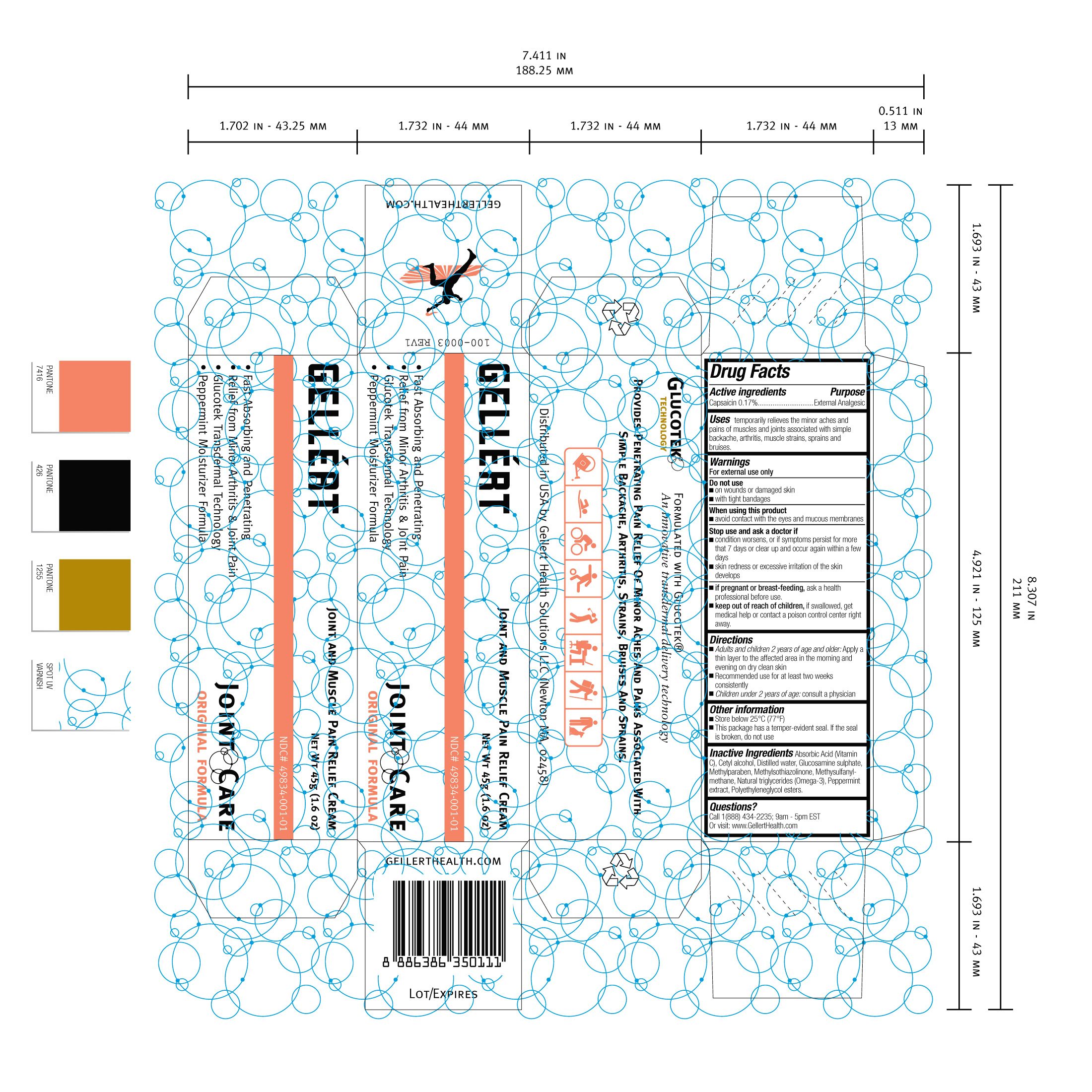 DRUG LABEL: Gellert Joint Care
NDC: 49834-001 | Form: CREAM
Manufacturer: Gellert Health Solutions LLC
Category: otc | Type: HUMAN OTC DRUG LABEL
Date: 20120301

ACTIVE INGREDIENTS: Capsaicin 0.17 g/100 g
INACTIVE INGREDIENTS: Water 73.748 g/100 g; Glucosamine Sulfate 8 g/100 g; Octanoic Acid 8 g/100 g; Glyceryl Monostearate 3 g/100 g; Butylene Glycol 1.8 g/100 g; Cetyl Alcohol 1.5 g/100 g; Dimethicone 0.8 g/100 g; Methylparaben 0.12 g/100 g; Peppermint Oil 0.05 g/100 g; Methylisothiazolinone 0.05 g/100 g; Curcumin 0.001 g/100 g; FD&C Yellow No. 5 0.006 g/100 g

Gellert Joint Care

Active ingredients

Capsaicin 0.17%

Purpose

External Analgesic

INDICATIONS AND USAGE

Uses temporarily relieves the minor aches and pains of muscles and joints associated with simple backache, arthritis, muscle strains, sprains and bruises.

Warnings

For external use only

Do Not Use

- on wounds or damaged skin
- with tight bandages

When using this product

- avoid contact with the eyes and mucous membranes

Stop use and ask a doctor if

- condition worsens, or if symptoms persist for more than 7 days or clear up and occur again within a few days
- skin redness or excessive irritation of the skin develops

PREGNANCY OR BREAST FEEDING

- if pregnant or breast-feeding, ask a health professional before use.

- keep out of reach of children, if swallowed, get medical help or contact a poison control center right away.

Directions

- Adults and children 2 years of age and older: Apply a thin layer to the affected area in the morning and evening on dry clean skin
- Recommended use for at least two weeks consistently
- Children under 2 years of age: consult a physician

Other information

- Store below 25°C (77°F)
- This package has a tamper-evident seal. If the seal is broken, do not use

INACTIVE INGREDIENT

Inactive Ingredients Ascorbic Acid (Vitamin C), Cetyl alcohol, Distilled water, Glucosamine sulphate, Methylparaben, Methylsothiazolinone, Methylsulfonylmethane, Natural triglycerides (Omega-3), Peppermit extract, Polyethyleneglycol esters.

Questions?

Call 1 (888) 434-2235; 9am - 5pm EST

Or visit: www.GellertHealth.com

PACKAGE LABEL

Principal Display Panel - Gellert Joint Care - 45g Carton